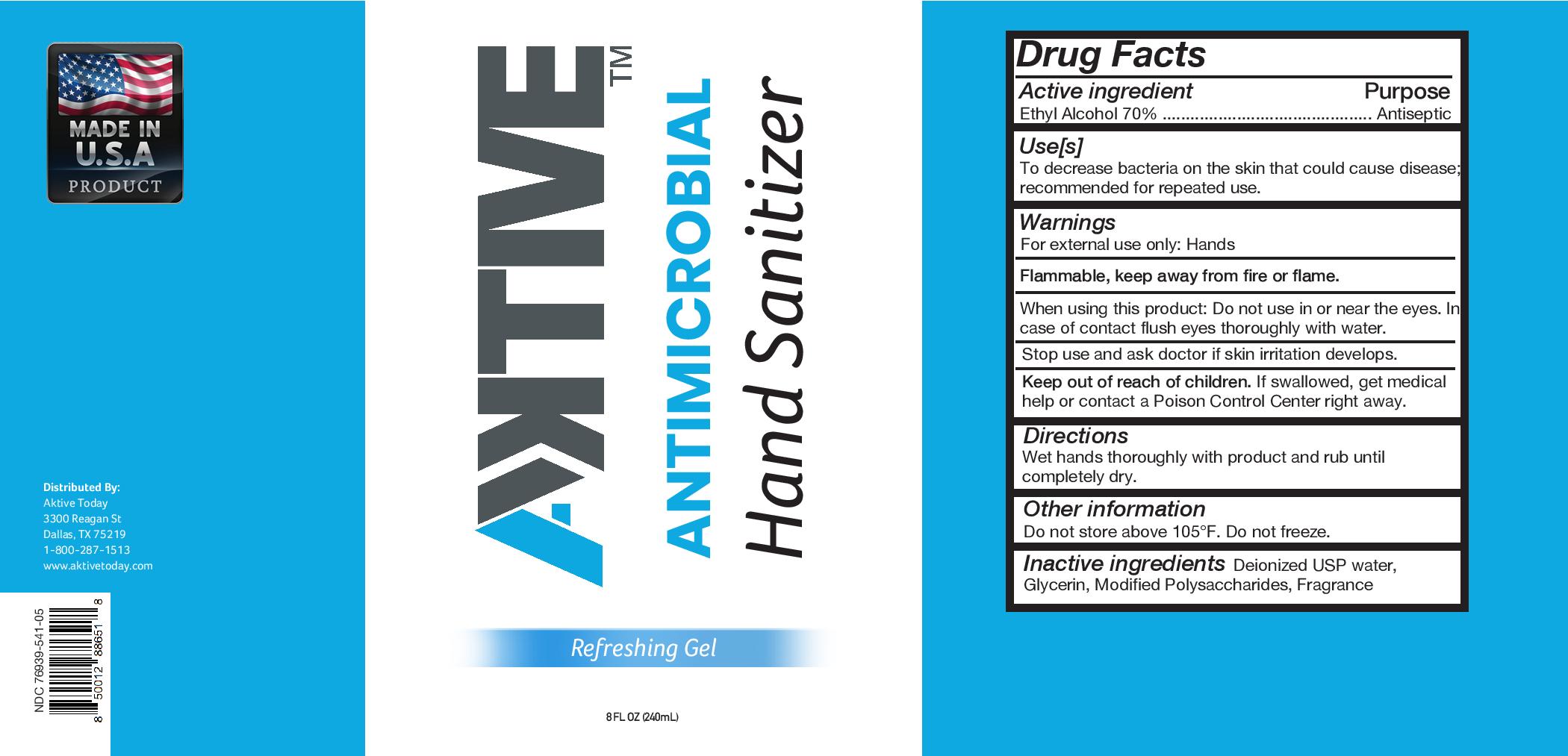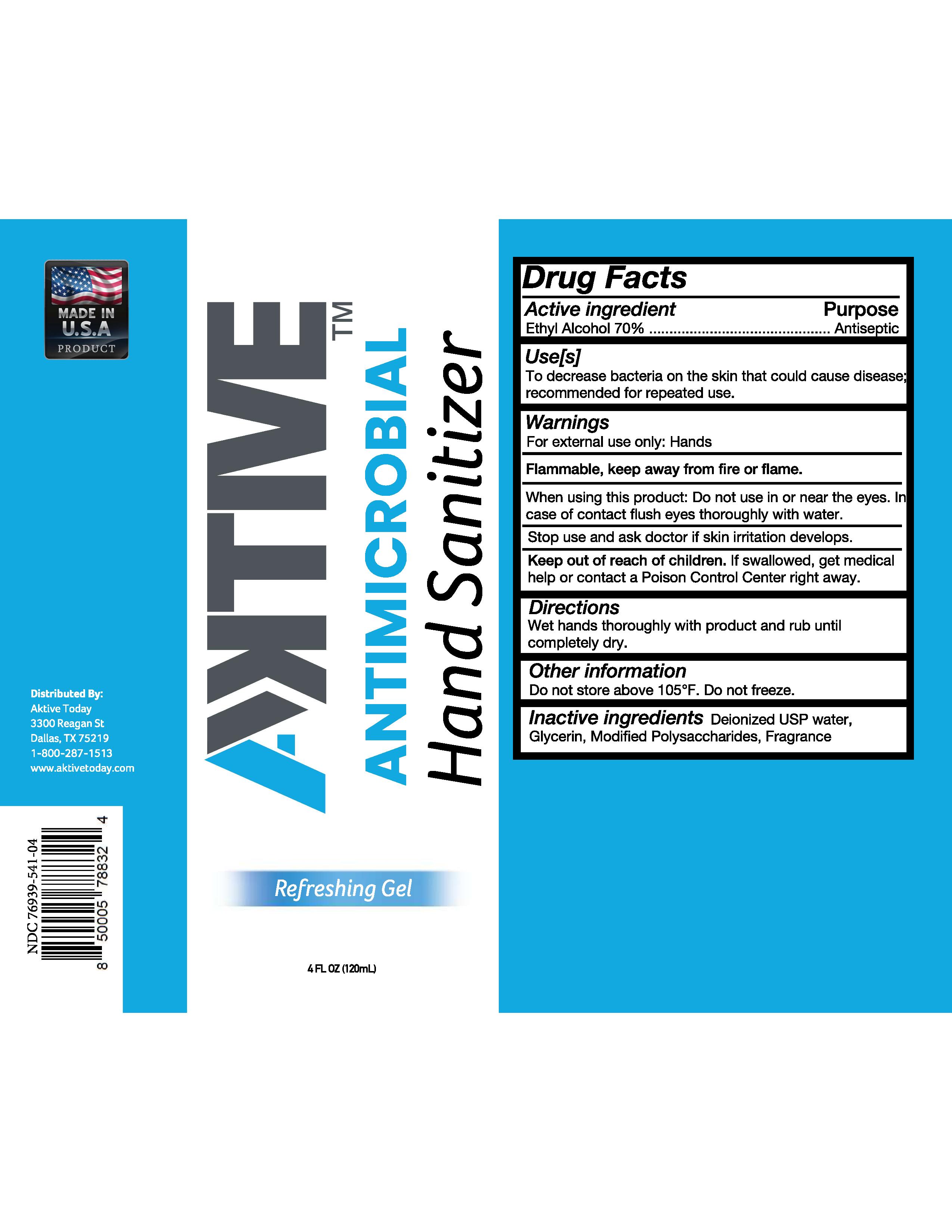 DRUG LABEL: Aktive Hand Sanitizer
NDC: 76939-541 | Form: LIQUID
Manufacturer: NVIP LLC
Category: otc | Type: HUMAN OTC DRUG LABEL
Date: 20230208

ACTIVE INGREDIENTS: ALCOHOL 80 mL/100 mL
INACTIVE INGREDIENTS: GLYCERIN 0.3 mL/100 mL; CARBOMER HOMOPOLYMER, UNSPECIFIED TYPE 0.3 mL/100 mL; WATER

Aktive Hand Sanitizer 541

This is a gel hand sanitizer manufactured with 70% ethanol as active ingredient according to the FDA monograph.

Active Ingredient(s)

Alcohol 70% v/v. Purpose: Antiseptic

Purpose

Antiseptic, Hand Sanitizer

Use

Hand Sanitizer to help reduce bacteria that potentially can cause disease. For use when soap and water are not available.

Warnings

For external use only. Flammable. Keep away from heat or flame

Do not use

- in children less than 2 months of age
- on open skin wounds

When using this product keep out of eyes, ears, and mouth. In case of contact with eyes, rinse eyes thoroughly with water.
Stop use and ask a doctor if irritation or rash occurs. These may be signs of a serious condition.
Keep out of reach of children. If swallowed, get medical help or contact a Poison Control Center right away.

Stop use and ask a doctor if irritation or rash occurs. These may be signs of a serious condition.

Keep out of reach of children. If swallowed, get medical help or contact a Poison Control Center right away.

Directions

- Place enough product on hands to cover all surfaces. Rub hands together until dry.
- Supervise children under 6 years of age when using this product to avoid swallowing.

Other information

- Store between 15-30C (59-86F)
- Avoid freezing and excessive heat above 40C (104F)

Inactive ingredients

glycerin, modified polysaccharides, purified water USP, fregrance

Package Label - Principal Display Panel

236 mL NDC: 76939-541-05

118ml NDC 76939-541-04